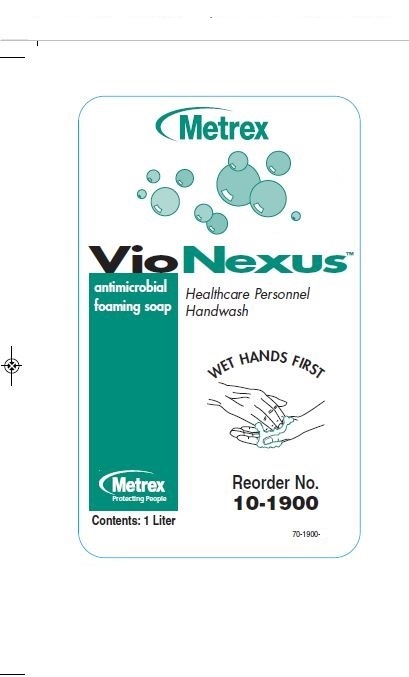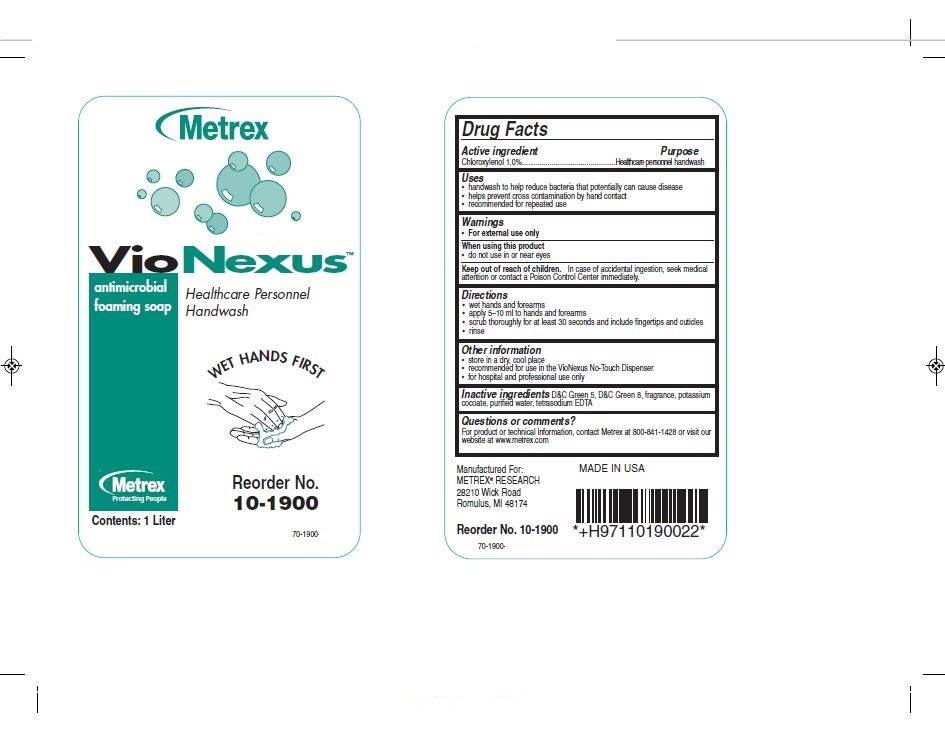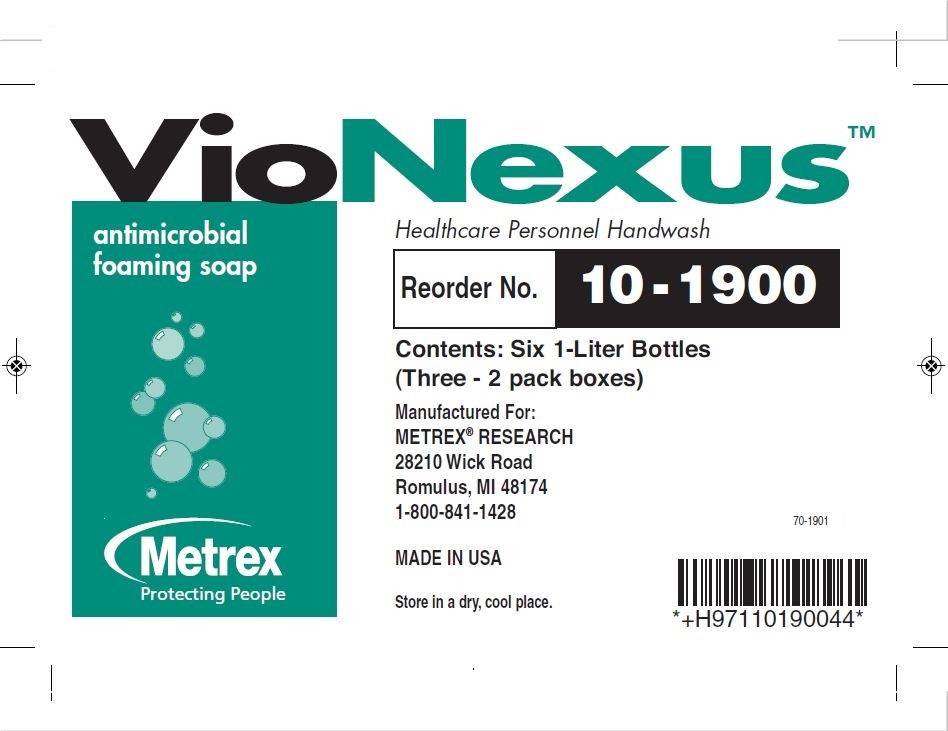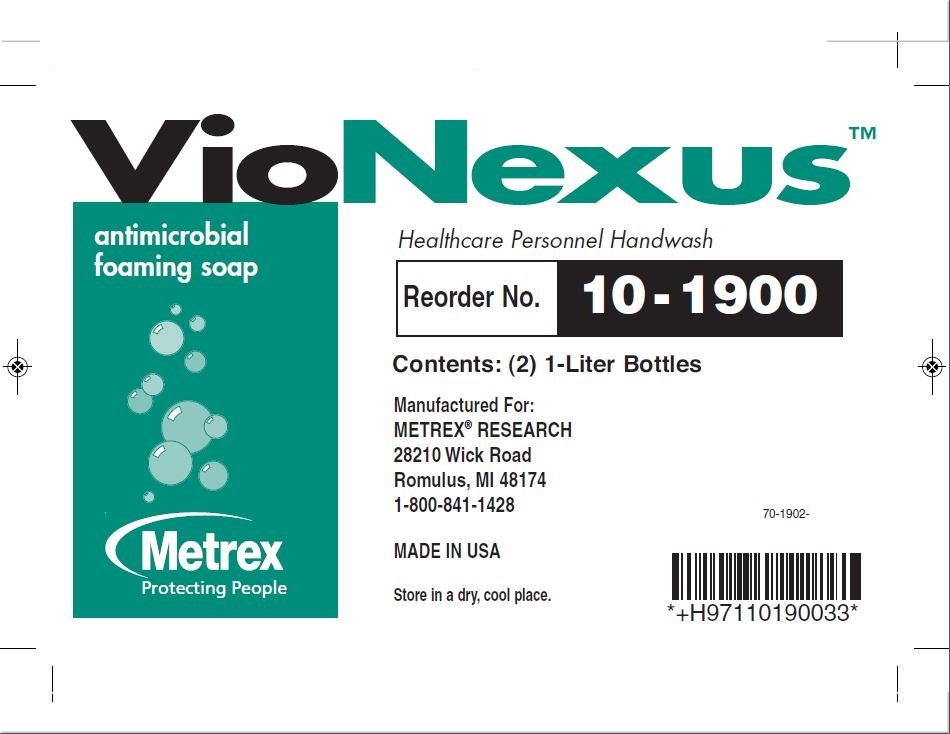 DRUG LABEL: VioNexus
NDC: 55443-0600 | Form: LIQUID
Manufacturer: Metrex Research, LLC
Category: otc | Type: HUMAN OTC DRUG LABEL
Date: 20241007

ACTIVE INGREDIENTS: CHLOROXYLENOL 1 g/100 mL
INACTIVE INGREDIENTS: WATER; EDETATE SODIUM; D&C GREEN NO. 8; D&C GREEN NO. 5; POTASSIUM COCOATE

VioNexus Antimicrobial Foaming Soap

Drug Facts

Active Ingredients Purpose

Chloroxylenol 1.0%................Healthcare personnel handwash

Uses

- handwash to help reduce bacteria that potentially can cause disease
- helps prevent cross contamination by hand contact
- recommended for repeated use

Warnings

For external use only

Keep out of reach of children

In case of accidental ingestion, seek medical attention or contact a poison control center immediately.

Directions

- wet hands and forearms
- apply 5-10 ml to hands and forearms
- scrub thoroughly for at least 30 seconds and include fingertips and cuticles
- rinse

Inactive Ingredients

D&C Green 5, D&C Green 8, fragrance, potassium cocoate, purified water, tetrasodium EDTA

INDICATIONS AND USAGE

Healthcare Personnel Handwash

Principal Display Panel

VioNexus

antimicrobial foaming soap

Healthcare Personnel Handwash

Manufactured for:

METREX RESEARCH

28210 Wick Road

Romulus, Michigan 48174

Reorder No.:

Metrex

Protecting People

Contents: 1 Liter